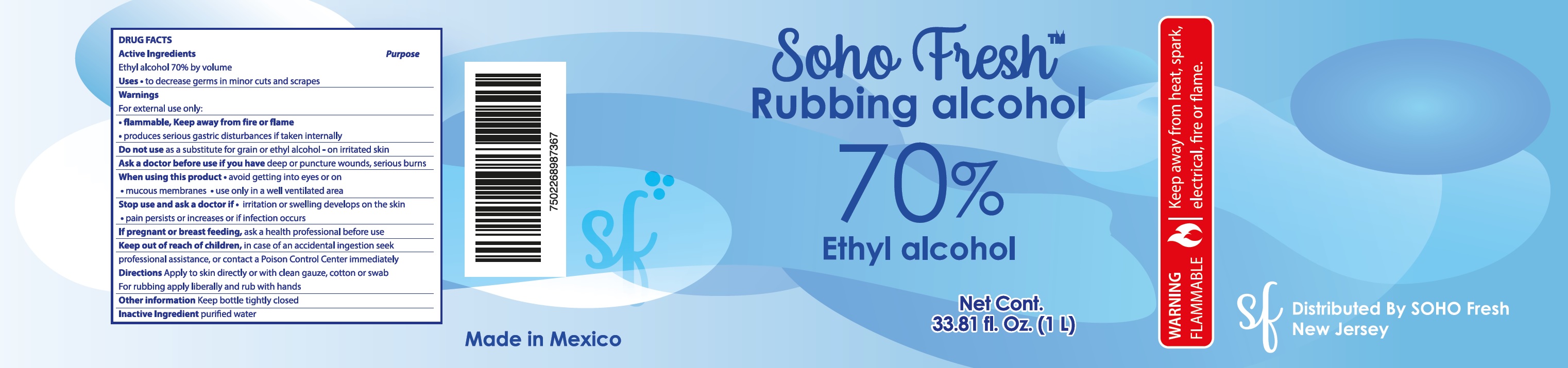 DRUG LABEL: Soho Fresh Rubbing Alcohol
NDC: 78533-001 | Form: LIQUID
Manufacturer: ESSAAR INC.
Category: otc | Type: HUMAN OTC DRUG LABEL
Date: 20200618

ACTIVE INGREDIENTS: ALCOHOL 0.7 1/1 mL
INACTIVE INGREDIENTS: WATER

Soho Fresh Rubbing Alcohol

Active Ingredients

Ethyl alcohol 70% by volume

Uses

- to decrease germs in minor cuts and scrapes

Warnings

For external use only: hands.

Flammable, Keep away from fire of flame.

- produce serious gastric disturbances if taken internally

Do not use

as a substitute for grain or ethyl alcohol-on irritated skin

Ask a doctor before use if you have

deep only or puncture wounds, serious burns

When using this product

- avoid getting into eyes or on
- mucous membranes
- use only in a well ventilated area

Stop use and ask a doctor if

- irritation or swelling develops on the skin
- pain persists or increase or if infection occurs

If pregnant or breast feeding,

ask a health professional before use

Keep out of reach of children,

in case of an accidental ingestion seek professional assistance, or contact a Poison Control Center immediately

Directions

Apply to skin directly or with clean gauze, cotton or swab

For rubbing apply liberally and rub with hands

Other information

Keep bottle tightly closed

Inactive Ingredient

purified water